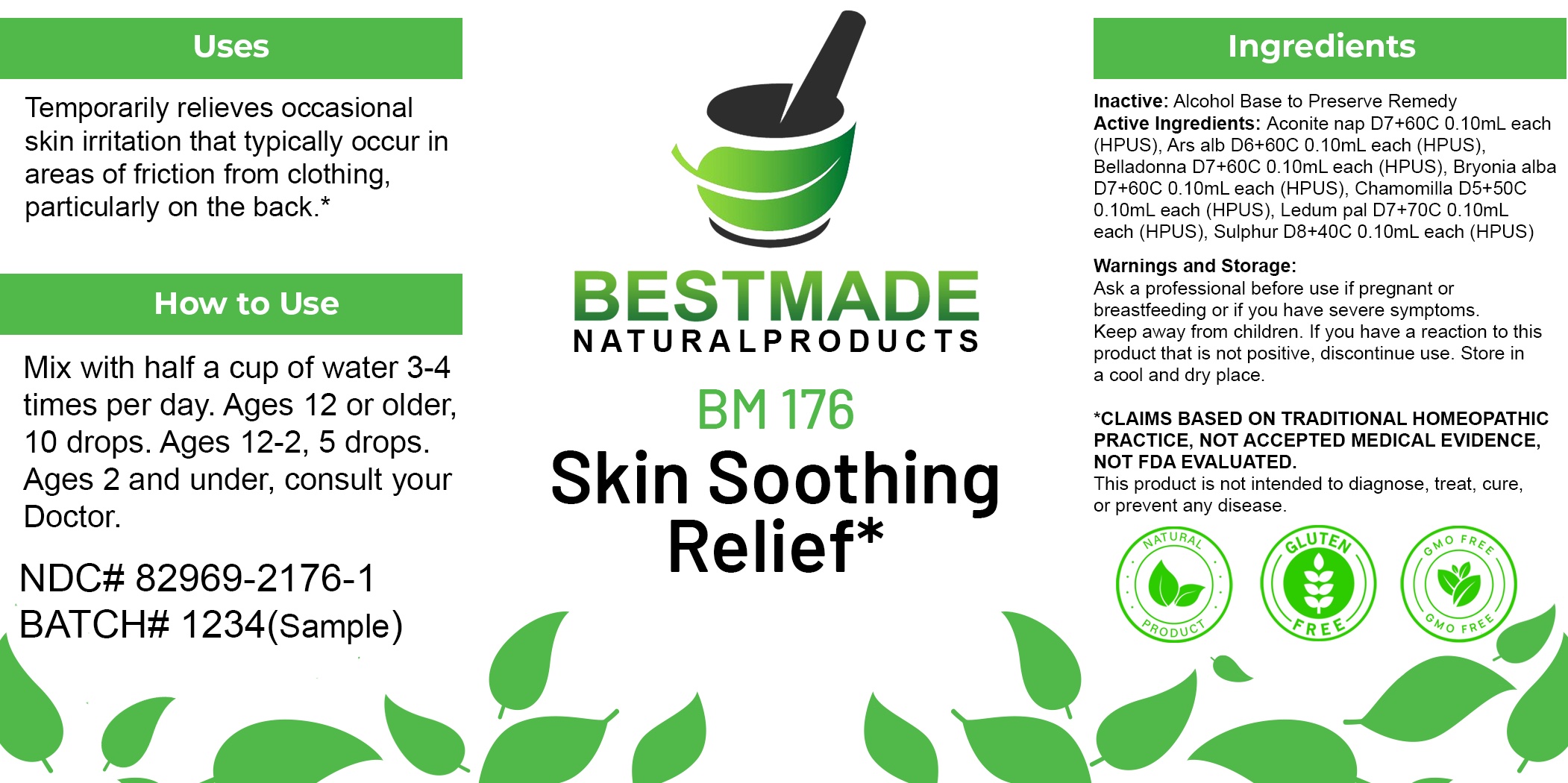 DRUG LABEL: Bestmade Natural Products BM176
NDC: 82969-2176 | Form: LIQUID
Manufacturer: Bestmade Natural Products
Category: homeopathic | Type: HUMAN OTC DRUG LABEL
Date: 20250219

ACTIVE INGREDIENTS: ACONITUM NAPELLUS WHOLE 30 [hp_C]/30 [hp_C]; BRYONIA ALBA ROOT 30 [hp_C]/30 [hp_C]; CHAMOMILE 30 [hp_C]/30 [hp_C]; RHODODENDRON TOMENTOSUM LEAFY TWIG 30 [hp_C]/30 [hp_C]; ATROPA BELLADONNA 30 [hp_C]/30 [hp_C]; SULFUR 30 [hp_C]/30 [hp_C]; ARSENIC TRIOXIDE 30 [hp_C]/30 [hp_C]
INACTIVE INGREDIENTS: ALCOHOL 30 [hp_C]/30 [hp_C]

BM176

DOSAGE AND ADMINISTRATION

How to Use

Mix with half a cup of water 3-4 times per day. Ages 12 or older, 10 drops. Ages 12-2, 5 drops. Ages 2 and under, consult your Doctor.

Inactive:

Alcohol Base to Preserve Product

ACTIVE INGREDIENT

INGREDIENTS IN NATURAL HEAT RASH REMEDY:

Aconite nap D7+60C 0.10mL each (HPUS), Ars alb D6+60C 0.10mL each (HPUS), Belladonna D7+60C 0.10mL each (HPUS), Bryonia alba D7+60C 0.10mL each (HPUS), Chamomilla D5+50C 0.10mL each (HPUS), Ledum pal D7+70C 0.10mL each (HPUS), Sulphur D8+40C 0.10mL each (HPUS)

Uses
Best used for heat rashes that typically occur in areas of friction from clothing, particularly on the back.

Uses
Best used for heat rashes that typically occur in areas of friction from clothing, particularly on the back.

KEEP OUT OF REACH OF CHILDREN

Warnings and Storage:

Ask a professional before use if pregnant or breastfeeding or if you have severe symptoms.

Keep away from children. If you have a reaction to this product that is not positive, discontinue use. Store in a cool and dry place

*CLAIMS BASED ON TRADITIONAL HOMEOPATHIC PRACTICE, NOT ACCEPTED MEDICAL EVIDENCE NOT FDA EVALUATED.
This product is not intended to diagnose, treat, cure, or prevent any disease.

Warnings and Storage:

Ask a professional before use if pregnant or breastfeeding or if you have severe symptoms.

Keep away from children. If you have a reaction to this product that is not positive, discontinue use. Store in a cool and dry place

*CLAIMS BASED ON TRADITIONAL HOMEOPATHIC PRACTICE, NOT ACCEPTED MEDICAL EVIDENCE NOT FDA EVALUATED.
This product is not intended to diagnose, treat, cure, or prevent any disease.

Entire package label